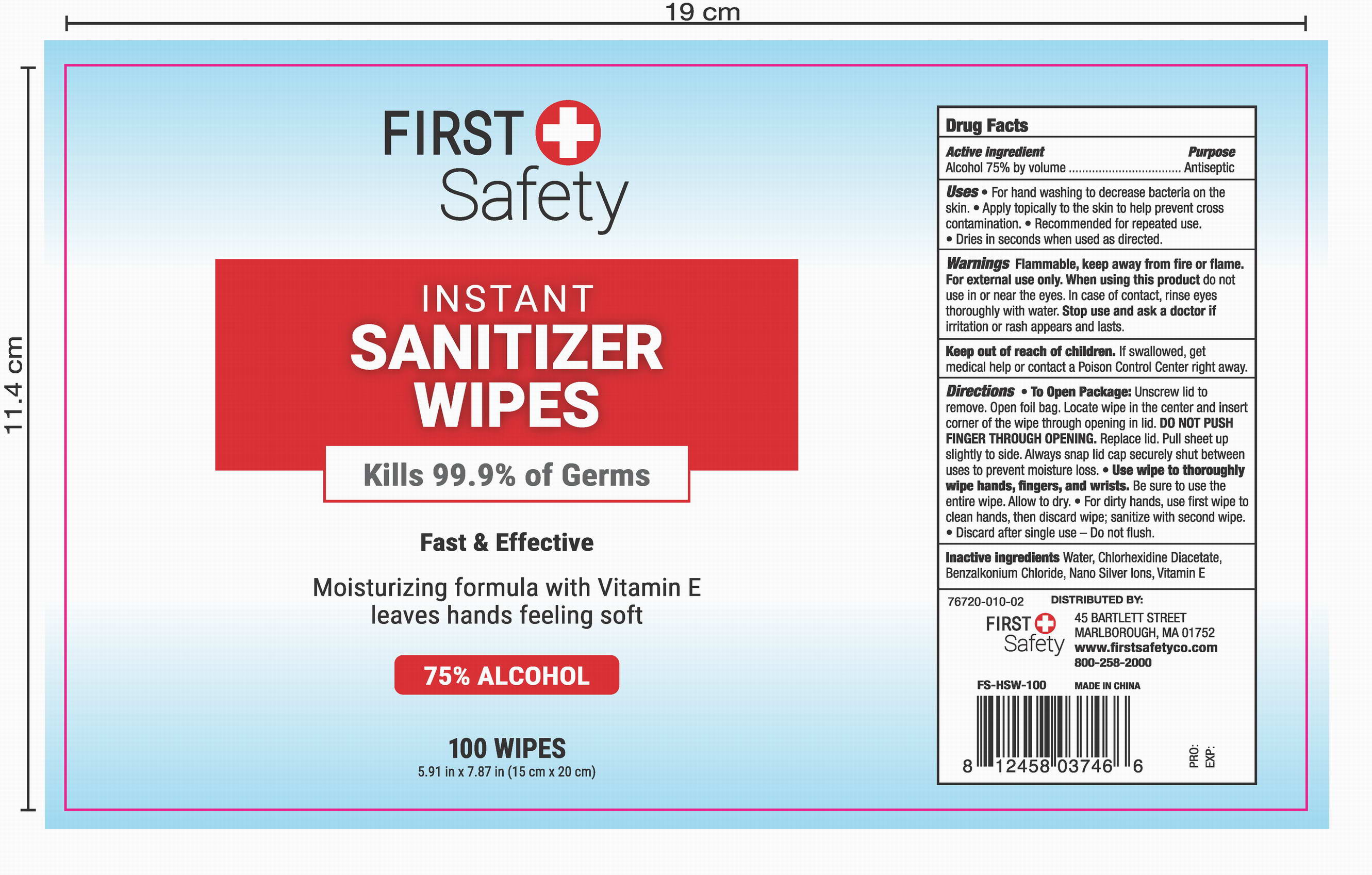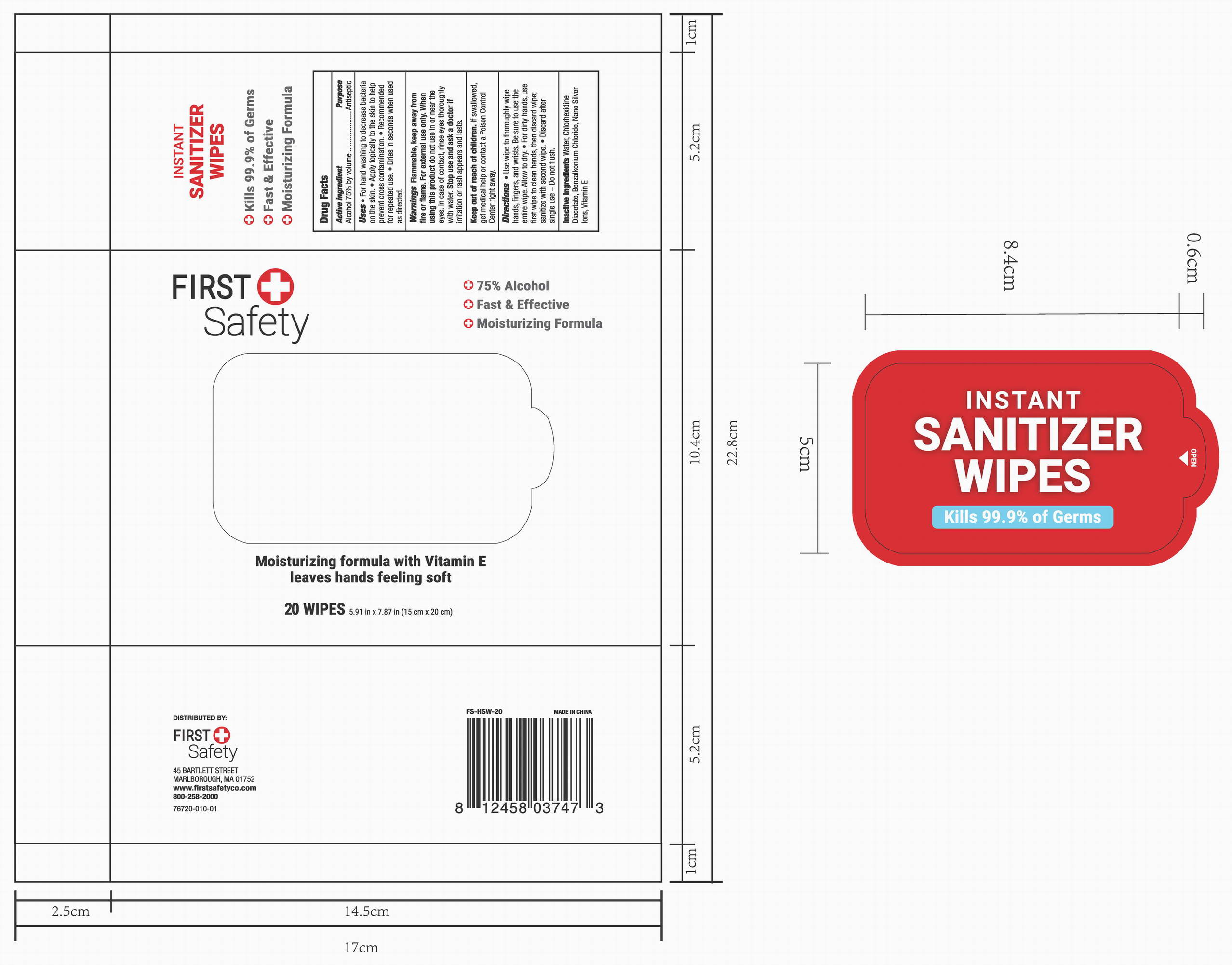 DRUG LABEL: Instant Sanitizing Wipes
NDC: 78183-003 | Form: CLOTH
Manufacturer: Kunming Ansheng Industry & Trade Co., Ltd.
Category: otc | Type: HUMAN OTC DRUG LABEL
Date: 20200702

ACTIVE INGREDIENTS: ALCOHOL 0.75 U/1 U
INACTIVE INGREDIENTS: SILVER ACETATE 0.00004 U/1 U; CHLORHEXIDINE ACETATE 0.001 U/1 U; BENZALKONIUM CHLORIDE 0.001 U/1 U; WATER

Instant Sanitizing Wipes

Active Ingredient(s)

Alcohol 75% v/v;

Chlorohexidine Diacetate 0.1% v/v;

Benzalkonium 0.1% v/v;

Purpose

Antibacterial

Use

• For hand washing to decrease bacteria on the skin.
• Apply topically to the skin to help prevent cross contamination.
• Recommended for repeated use.
• Dries in seconds when used as directed.

Warnings

For external use only. Flammable. Keep away from heat or flame

Do not use

- on infants less than 2 months of age
- on open skin wounds

When using this product keep out of eyes, ears, and mouth. In case of contact with eyes, rinse eyes thoroughly with water.

Stop use and ask a doctor if irritation or rash appears and lasts.

Keep out of reach of children. If swallowed, get medical help or contact a Poison Control Center right away.

Directions

• To Open Package: Unscrew lid to remove.
• Open foil bag.
• Locate wipe in the center and insert corner of the wipe through opening in lid.
• DO NOT PUSH FINGER THROUGH OPENING.
• Replace lid.
• Pull sheet up slightly to side. Always snap lid cap securely shut between uses to prevent moisture loss.

Other information

- Store between 15-30℃ (59-86F)
- Avoid freezing and excessive heat about 40℃ (104F)

Inactive ingredients

Water, Chlorhexidine Diacetate, Benzalkonium Chloride, Nano Silver Ions, Vitamin E

Package Label - Principal Display Panel

20 wipes in 1 bag. NDC: 78183-003-01;

100 wipes in 1 bag. NDC: 78183-003-02;